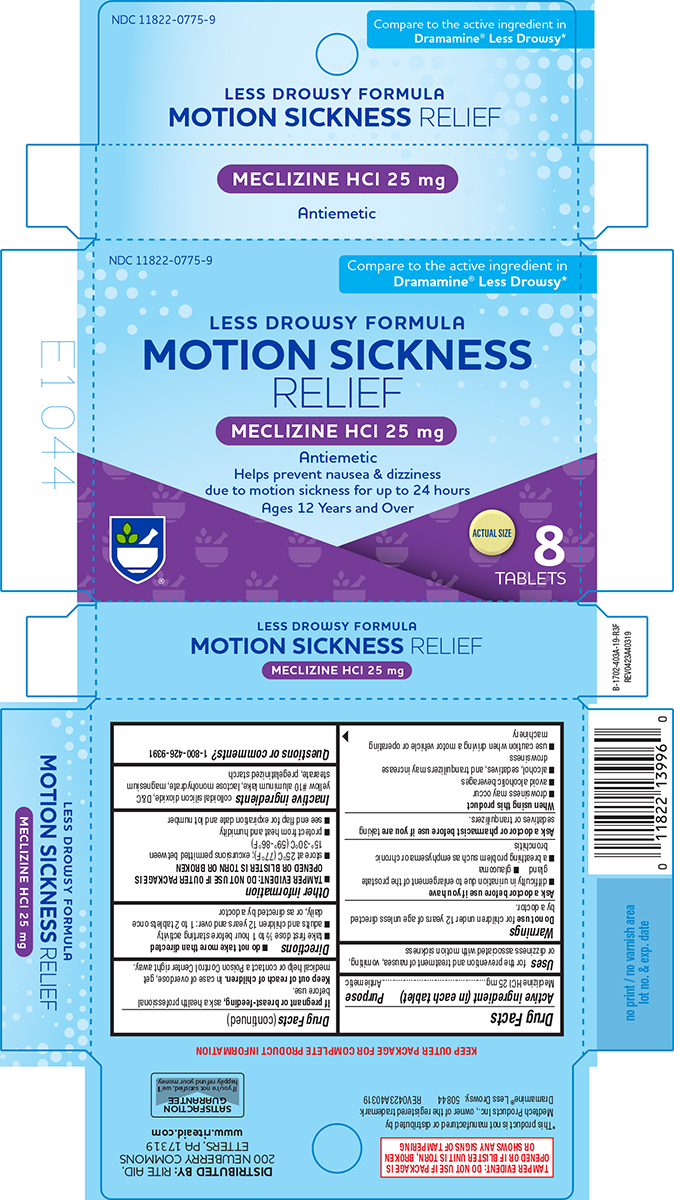 DRUG LABEL: Less Drowsy Motion Sickness Relief
NDC: 11822-0775 | Form: TABLET
Manufacturer: Rite Aid Corporation
Category: otc | Type: HUMAN OTC DRUG LABEL
Date: 20260109

ACTIVE INGREDIENTS: MECLIZINE HYDROCHLORIDE 25 mg/1 1
INACTIVE INGREDIENTS: SILICON DIOXIDE; D&C YELLOW NO. 10 ALUMINUM LAKE; LACTOSE MONOHYDRATE; MAGNESIUM STEARATE; STARCH, CORN

Rite Aid 44-403A

Active ingredient (in each tablet)

Meclizine HCl 25 mg

Purpose

Antiemetic

Uses

for the prevention and treatment of nausea, vomiting, or dizziness associated with motion sickness

Warnings

Do not use

for children under 12 years of age unless directed by a doctor.

Ask a doctor before use if you have

- glaucoma
- difficulty in urination due to enlargement of the prostate gland
- a breathing problem such as emphysema or chronic bronchitis

Ask a doctor or pharmacist before use if you are

taking sedatives or tranquilizers.

When using this product

- drowsiness may occur
- avoid alcoholic beverages
- alcohol, sedatives, and tranquilizers may increase drowsiness
- use caution when driving a motor vehicle or operating machinery

If pregnant or breast-feeding,

ask a health professional before use.

Keep out of reach of children.

In case of overdose, get medical help or contact a Poison Control Center right away.

Directions

- do not take more than directed
- take first dose 1/2 to 1 hour before starting activity
- adults and children 12 years and over: 1 to 2 tablets once daily, or as directed by a doctor

Other information

- TAMPER EVIDENT: DO NOT USE IF OUTER PACKAGE IS OPENED OR BLISTER IS TORN OR BROKEN
- store at 25ºC (77ºF); excursions permitted between 15º-30ºC (59º-86ºF)
- protect from heat and humidity
- see end flap for expiration date and lot number

Inactive ingredients

colloidal silicon dioxide, D&C yellow #10 aluminum lake, lactose monohydrate, magnesium stearate, pregelatinized starch

Questions or comments?

1-800-426-9391

Principal Display Panel

NDC 11822-0775-9

Compare to the active ingredient in
Dramamine® Less Drowsy*

LESS DROWSY FORMULA
MOTION SICKNESS
RELIEF
MECLIZINE HCl 25 mg
Antiemetic
Helps prevent nausea & dizziness
due to motion sickness for up to 24 hours
Ages 12 Years and Over

8
TABLETS

ACTUAL SIZE

TAMPER EVIDENT: DO NOT USE IF PACKAGE IS
OPENED OR IF BLISTER UNIT IS TORN, BROKEN
OR SHOWS ANY SIGNS OF TAMPERING

*This product is not manufactured or distributed by
Medtech Products Inc., owner of the registered trademark
Dramamine® Less Drowsy. 50844 REV0423A40319

DISTRIBUTED BY: RITE AID,
200 NEWBERRY COMMONS
ETTERS, PA 17319
www.riteaid.com

SATISFACTION
GUARANTEE
If you're not satisfied, we'll
happily refund your money.

Rite Aid 44-403A